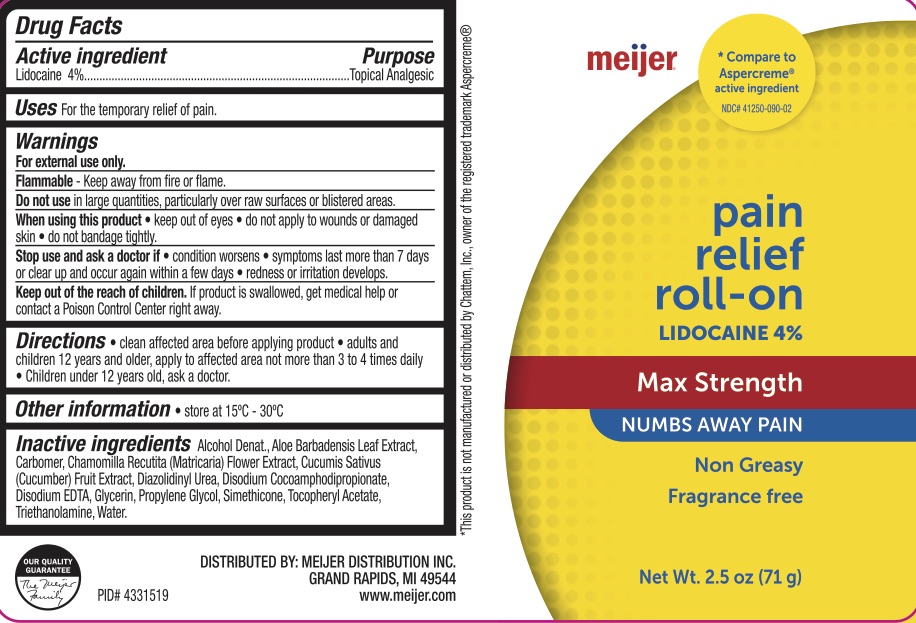 DRUG LABEL: Meijer Pain Relief
NDC: 79481-0989 | Form: LIQUID
Manufacturer: Meijer
Category: otc | Type: HUMAN OTC DRUG LABEL
Date: 20241220

ACTIVE INGREDIENTS: LIDOCAINE 4 g/100 g
INACTIVE INGREDIENTS: CUCUMBER; DIAZOLIDINYL UREA; PROPYLENE GLYCOL; TROLAMINE; DISODIUM COCOAMPHODIPROPIONATE; WATER; CHAMOMILE; GLYCERIN; ALOE VERA LEAF; CARBOMER INTERPOLYMER TYPE A (ALLYL SUCROSE CROSSLINKED); ALPHA-TOCOPHEROL ACETATE

Meijer Pain Relief Roll-on

ACTIVE INGREDIENT

Lidocaine 4%

PURPOSE

Topical Analgesic

INDICATIONS AND USAGE

For the temporary relief of pain.

WARNINGS

For external use only. Flammable--Do not use while smoking or near heat or flame. When using this product avoid contact with eyes, do not apply to wounds or damaged skin, and do not bandage tightly. Stop use and ask a doctor if condition worsens, if symptoms persist for more than 7 days or clear up and occur again within a few days.

KEEP OUT OF REACH OF CHILDREN

If swallowed, get medical help or contact a Poison Control Center right away.

DOSAGE AND ADMINISTRATION

Clean affected area before applying product. Adults and children 12 years of age and older, apply to the affected area not more than 3 to 4 times daily. Children under 12 years old ask a doctor.

INACTIVE INGREDIENT

Alcohol Denat., Aloe Barbadensis Leaf Extract, Carbomer, Chamomilla Recutita (Matricaria) Flower Extract, Cucumis Sativus (Cucumber) Fruit Extract, Diazolidinyl Urea, Disodium Cocoamphodipropionate, Disodium EDTA, Glycerin, Propylene Glycol, Simethicone, Tocopheryl Acetate, Triethanolamine, Water.